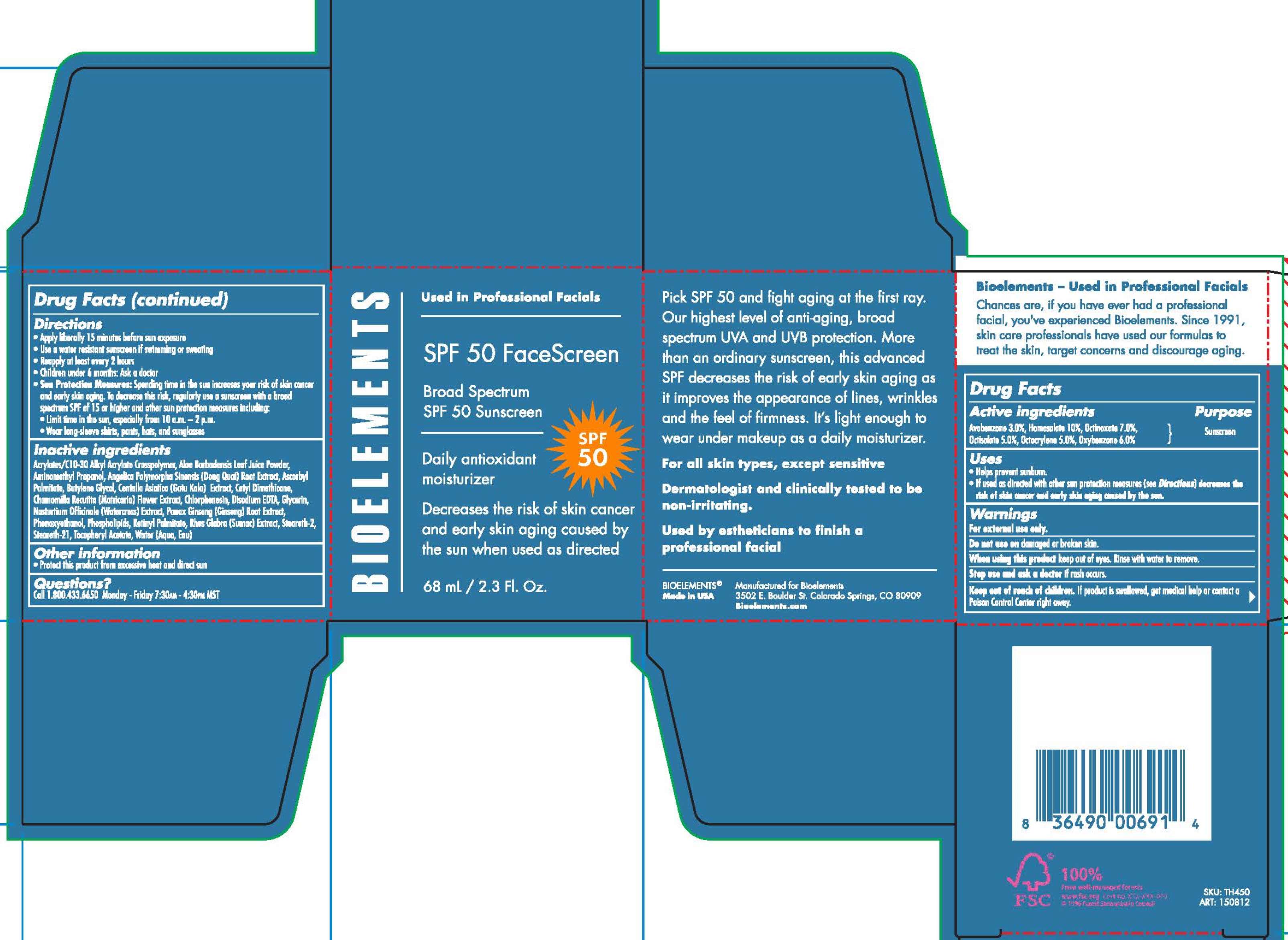 DRUG LABEL: SPF 50 Face Sunscreen
NDC: 49825-201 | Form: CREAM
Manufacturer: Bioelements, Inc
Category: otc | Type: HUMAN OTC DRUG LABEL
Date: 20251217

ACTIVE INGREDIENTS: AVOBENZONE 3 g/100 mL; HOMOSALATE 10 g/100 mL; OCTINOXATE 7 g/100 mL; OCTISALATE 5 g/100 mL; OCTOCRYLENE 5 g/100 mL; OXYBENZONE 6 g/100 mL
INACTIVE INGREDIENTS: CARBOMER INTERPOLYMER TYPE A (ALLYL SUCROSE CROSSLINKED); ALOE VERA LEAF; AMINOMETHYLPROPANOL; ANGELICA SINENSIS ROOT; ASCORBYL PALMITATE; BUTYLENE GLYCOL; CENTELLA ASIATICA; CETYL DIMETHICONE 25; CHAMOMILE; CHLORPHENESIN; EDETATE DISODIUM; GLYCERIN; NASTURTIUM OFFICINALE; ASIAN GINSENG; PHENOXYETHANOL; LECITHIN, SOYBEAN; VITAMIN A PALMITATE; STEARETH-2; STEARETH-21; .ALPHA.-TOCOPHEROL ACETATE; WATER

SPF 50 Face Sunscreen

Active Ingredients Purpose

Avobenozone 3.0% ............. Sunscreen

Homosalate 10% .............. Sunscreen

Octinoxate 7.0% ............... Sunscreen

Octisalate 5.0% ................ Sunscreen

Octocrylene 5.0% ............. Sunscreen

Oxybenzone 6.0% ............. Sunscreen

Uses

- Helps prevent sunburn.
- If used as directed with other sun protection measures (see Directions) decreases the risk of skin cancer and early skin aging caused by the sun

Keep out of reach of children. If product is swallowed, get medical help or contact a Poison Control Center right away

Stop use and ask a doctor if rash occurs

Warnings

- For external use only
- Do not use on damaged or broken skin
- When using this product keep out of eyes. Rinse with water to remove.

Directions

- Apply liberally 15 minutes before sun exposure
- Use a water resistant sunscreen if swimming or sweating
- Reapply at least every 2 hours
- Children under 6 months: Ask a doctor
- Sun Protection Measures:Spending time in the sun increases your risk of skin cancer and early skin aging. To decrease this risk, regularly use a sunscreen with a broad spectrum SPF of 15 or higher and other sun protection measures including:
- Limit time in the sun, especially from 10a.m. - 2p.m.
- Wear long-sleeved shirts, pants, hats, and sunglasses

INACTIVE INGREDIENT

Acrylates/C10-30 Alkyl Acrylate Crosspolymer, Aloe Barbadensis Leaf Juice Powder, Aminomethyl Propanol, Angelica Polymorpha Sinensis (Dong Quai) Root Extract, Ascorbyl Palmitate, Buylene Glycol, Centella Asiatica (Gotu Kola) Extract, Cetyl Dimethicone, Chamomilla Recutita (Matricaria) Flower Extract, Chlorphenesin, Disodium EDTA, Glycerin, Nasturtium Officinale (Watercress) Extract, Panax Ginseng (Genseng) Root Extract, Phenoxyethanol, Phospholipids, Retinyl Palmitate, Rhus Glabra (Sumac) Extract, Steareth-2, Steareth-21, Tocopheryl Acetate, Water (Aqua, Eau)

PACKAGE LABEL

Bioelements

SPF 50 FaceScreen

Broad Spectrum

SPF 50 Sunsceen

Daily anitioxidant moisturizer

68 mL/ 2.3 Fl. Oz.